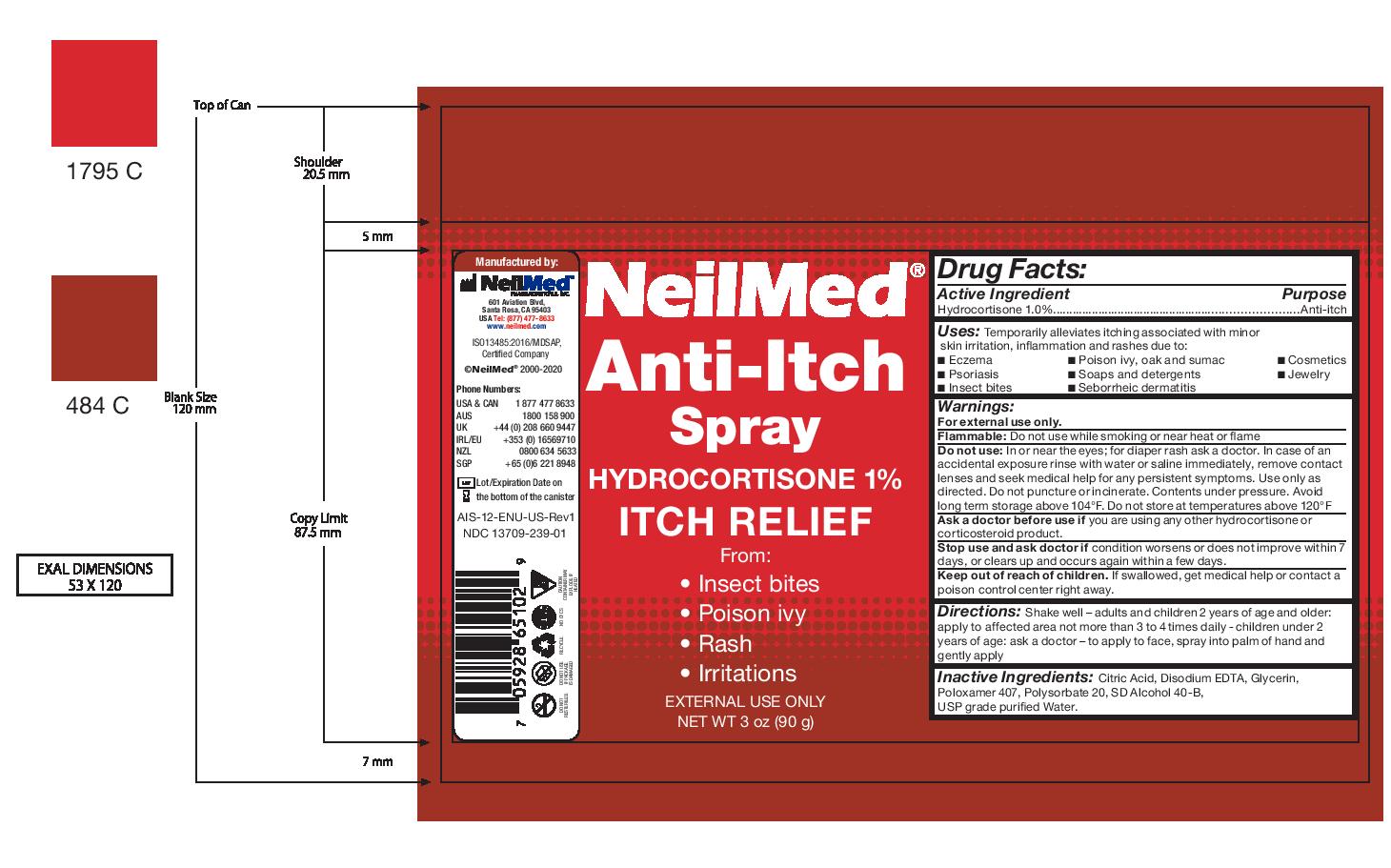 DRUG LABEL: NeilMed Anti-Itch
NDC: 13709-239 | Form: SPRAY
Manufacturer: NeilMed Pharmaceuticals Inc.
Category: otc | Type: HUMAN OTC DRUG LABEL
Date: 20240111

ACTIVE INGREDIENTS: HYDROCORTISONE 1 g/1 g
INACTIVE INGREDIENTS: EDETATE DISODIUM; ANHYDROUS CITRIC ACID; ALCOHOL; POLYSORBATE 20; GLYCERIN; POLOXAMER 407

NeilMed Anti-Itch Spray

Directions:

Shake well – adults and children 2 years of age and older: apply to affected area not more than 3 to 4 times daily - children under 2
years of age: ask a doctor – to apply to face, spray into palm of hand and gently apply

Warnings:

For external use only.
Flammable: Do not use while smoking or near heat or flame
Do not use: In or near the eyes; for diaper rash ask a doctor. In case of an accidental exposure rinse with water or saline immediately, remove contact lenses and seek medical help for any persistent symptoms. Use only as directed. Do not puncture or incinerate. Contents under pressure. Avoid long term storage above 104°F. Do not store at temperatures above 120°F
Ask a doctor before use if you are using any other hydrocortisone or corticosteroid product.
Stop use and ask doctor if condition worsens or does not improve within 7 days, or clears up and occurs again within a few days.
Keep out of reach of children. If swallowed, get medical help or contact a poison control center right away.

Inactive Ingredients:

Citric Acid, Disodium EDTA, Glycerin,Poloxamer 407, Polysorbate 20, SD Alcohol 40-B,USP grade purified Water.

Uses:

Temporarily alleviates itching associated with minor skin irritation, inflammation and rashes due to:

- Eczema ,
- Poison ivy, oak and sumac
- Cosmetics
- Psoriasis
- Soaps and detergents
- Jewelry
- Insect bites
- Seborrheic dermatitis

Keep out of reach of children.

If swallowed, get medical help or contact a poison control center right away.

Drug Facts: Purpose

Anti-itch

Drug Facts:

Active Ingredient
Hydrocortisone 1.0%